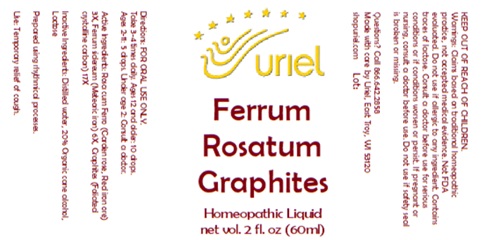 DRUG LABEL: Ferrum rosatum Graphites
NDC: 48951-4064 | Form: LIQUID
Manufacturer: Uriel Pharmacy Inc.
Category: homeopathic | Type: HUMAN OTC DRUG LABEL
Date: 20250627

ACTIVE INGREDIENTS: SEDUM ROSEUM WHOLE 3 [hp_X]/1 mL; FERRIC OXIDE RED 3 [hp_X]/1 mL; IRON 6 [hp_X]/1 mL; GRAPHITE 17 [hp_X]/1 mL
INACTIVE INGREDIENTS: WATER; ALCOHOL; LACTOSE

Ferrum rosatum Graphites

INDICATIONS AND USAGE

Directions: FOR ORAL USE ONLY.

DOSAGE AND ADMINISTRATION

Take 3-4 times daily. Ages 12 and older: 10 drops. Ages 2-11: 5 drops. Under age 2: Consult a doctor.

ACTIVE INGREDIENT

Active Ingredients: Rosa cum Ferro (Garden rose, Red iron ore) 3X, Ferrum sidereum (Meteoric iron) 6X, Graphites (Foliated crystalline carbon) 17X

Inactive Ingredients: Distilled water, Organic cane alcohol, Lactose

Prepared using rhythmical processes.

PURPOSE

Use: Temporary relief of cough.

KEEP OUT OF REACH OF CHILDREN.

WARNINGS

Warnings: Claims based on traditional homeopathic practice, not accepted medical evidence. Not FDA evaluated. Do not use if allergic to any ingredient. Contains traces of lactose. Consult a doctor before use for serious conditions or if conditions worsen or persist. If pregnant or nursing, consult a doctor before use. Do not use if safety seal is broken or missing.

Questions? Call 866.642.2858
Made with care by Uriel, East Troy, WI 53120
shopuriel.com Lot: